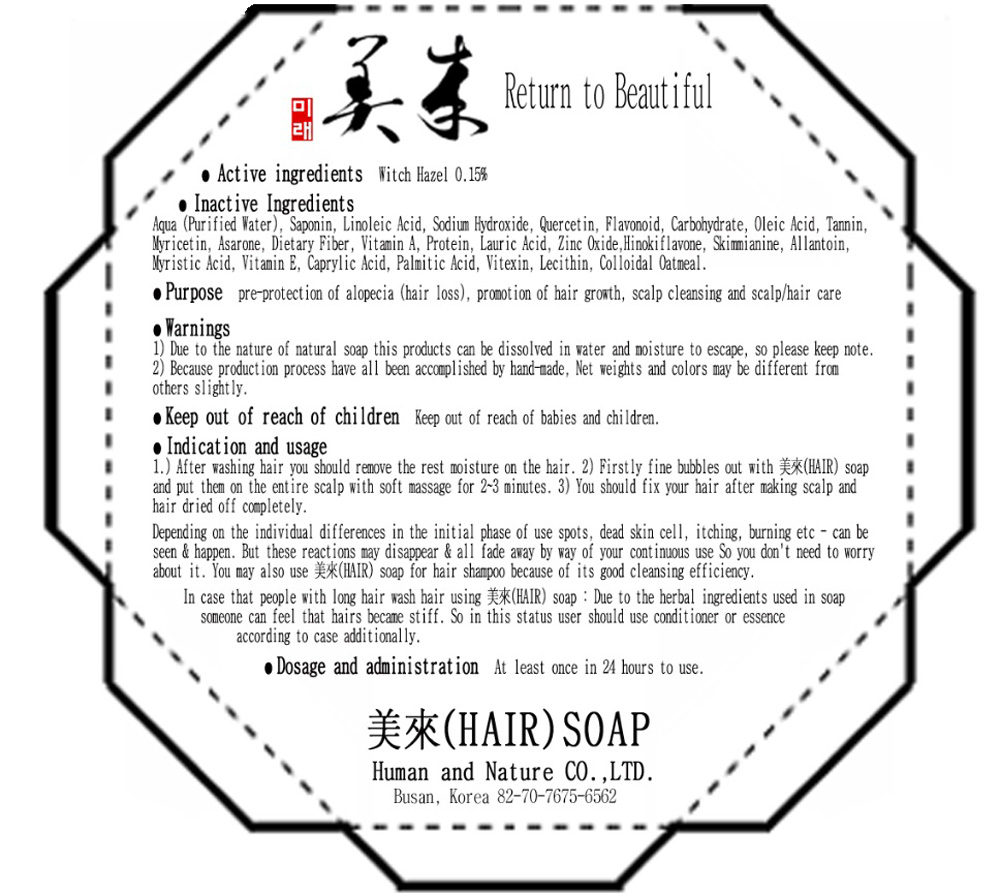 DRUG LABEL: MIRAE HAIR
NDC: 43071-110 | Form: SOAP
Manufacturer: HUMAN AND NATURE
Category: otc | Type: HUMAN OTC DRUG LABEL
Date: 20181219

ACTIVE INGREDIENTS: WITCH HAZEL 0.225 g/150 g
INACTIVE INGREDIENTS: WATER; ALLANTOIN

Drug Facts

Active Ingredient

Active ingredient: WITCH HAZEL 0.15%

Inactive Ingredients

Aqua (Purified Water), Saponin, Linoleic Acid, Sodium Hydroxide, Quercetin, Flavonoid, Carbohydrate, Oleic Acid, Tannin, Myricetin, Asarone, dietary fiber, Vitamin A, Protein, Lauric Acid, Zinc Oxide, Hinokiflavone, Skimmianine, Allantoin, Myristic Acid, Vitamin E, Caprylic Acid, Palmitic Acid, Vitexin, Lecithin, Colloidal Oatmeal

Purpose

Purpose: Pre-protection of alopecia (Hair loss), Promotion of hair growth, scalp cleansing and scalp/hair care

Warnings

Due to the nature of natural soap this products can be dissolved in water and moisture to escape, so please keep note.
Because production process have all been accomplished by hand-made, Net weights and colors may be different from others slightly.

Keep out of reach of children

Keep out of reach of babies and children.

Uses

Indication and usage:
1. After washing hair you should remove the rest moisture on the hair.
2. Firstly fine bubbles out with HAIR soap and put them on the entire scalp with soft massage for 2-3 minutes.
3. You should fix your hair after making scalp and hair dried off completely.

Directions

Dosage and administration:
At least once in 24 hours to use.